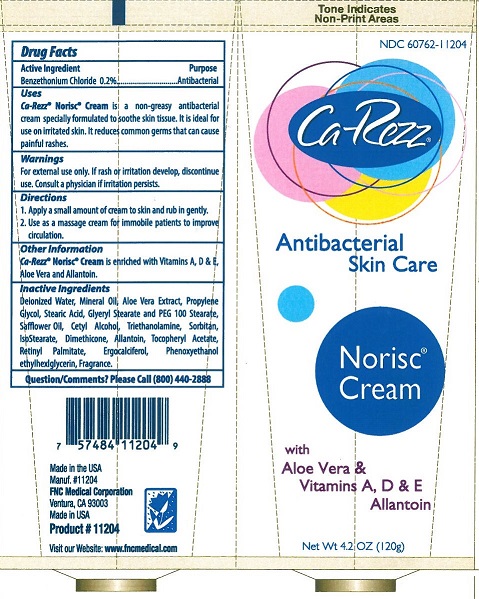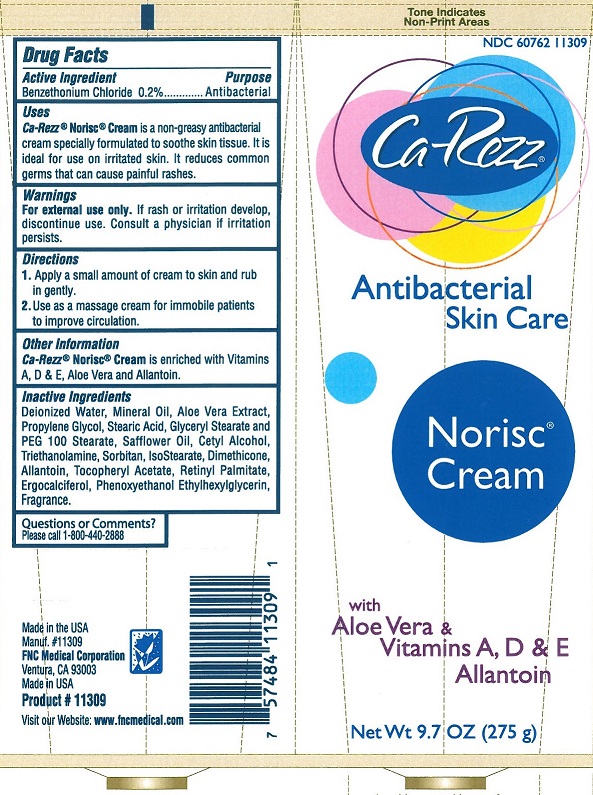 DRUG LABEL: CA-REZZ NORISC
NDC: 60762-112 | Form: CREAM
Manufacturer: FNC MEDICAL CORPORATION
Category: otc | Type: HUMAN OTC DRUG LABEL
Date: 20251022

ACTIVE INGREDIENTS: BENZETHONIUM CHLORIDE 0.2 g/100 g
INACTIVE INGREDIENTS: WATER; MINERAL OIL; ALOE VERA WHOLE; PROPYLENE GLYCOL; STEARIC ACID; GLYCERYL MONOSTEARATE; PEG-100 STEARATE; SAFFLOWER OIL; CETYL ALCOHOL; TROLAMINE; SORBITAN ISOSTEARATE; DIMETHICONE; ALLANTOIN; .ALPHA.-TOCOPHEROL ACETATE; VITAMIN A PALMITATE; ERGOCALCIFEROL; PHENOXYETHANOL; ETHYLHEXYLGLYCERIN

FNC - CA-REZZ - NORISC CREAM - ANTIBACTERIAL SKIN CARE (60762-112)

ACTIVE INGREDIENT

BENZETHONIUM CHLORIDE 0.2%

PURPOSE

ANTIBACTERIAL

USES

CA-REZZ NORSIC CREAM IS A NON-GREASY ANTIBACTERIAL CREAM SPECIALLY FORMULATED TO SOOTHE SKIN TISSUE. IT IS IDEAL FOR USE ON IRRITATED SKIN. IT REDUCES COMMON GERMS THAT CAN CAUSE PAINFUL RASHES.

WARNINGS

FOR EXTERNAL USE ONLY. IF RASH OR IRRITATION DEVELOP, DISCONTINUE USE. CONSULT A PHYSICIAN IF IRRITATION PERSISTS.

KEEP OUT OF REACH OF CHILDREN.

DIRECTIONS

1. APPLY A SMALL AMOUNT OF CREAM TO SKIN AND RUB GENTLY.
2. USE AS A MASSAGE CREAM FOR IMMOBILE PATIENTS TO IMPROVE CIRCULATION.

OTHER INFORMATION

CA-REZZ NORSIC CREAM IS ENRICHED WITH VITAMINS A, D & E, ALOE VERA AND ALLANTOIN.

INACTIVE INGREDIENTS

DEIONIZED WATER, MINERAL OIL, ALOE VERA EXTRACT, PROPYLENE GLYCOL, STEARIC ACID, GLYCERYL STEARATE AND PEG 100 STEARATE, SAFFLOWER OIL, CETYL ALCOHOL, TRIETHANOLAMINE, SORBITAN, ISOSTEARATE, DIMETHICONE, ALLANTOIN, TOCOPHERYL ACETATE, RETINYL PALMITATE, ERGOCALCIFEROL, PHENOXYETHANOL, ETHYLHEXYLGLYCERIN, FRAGRANCE.

QUESTIONS/COMMENTS?

PLEASE CALL (800) 440-2888